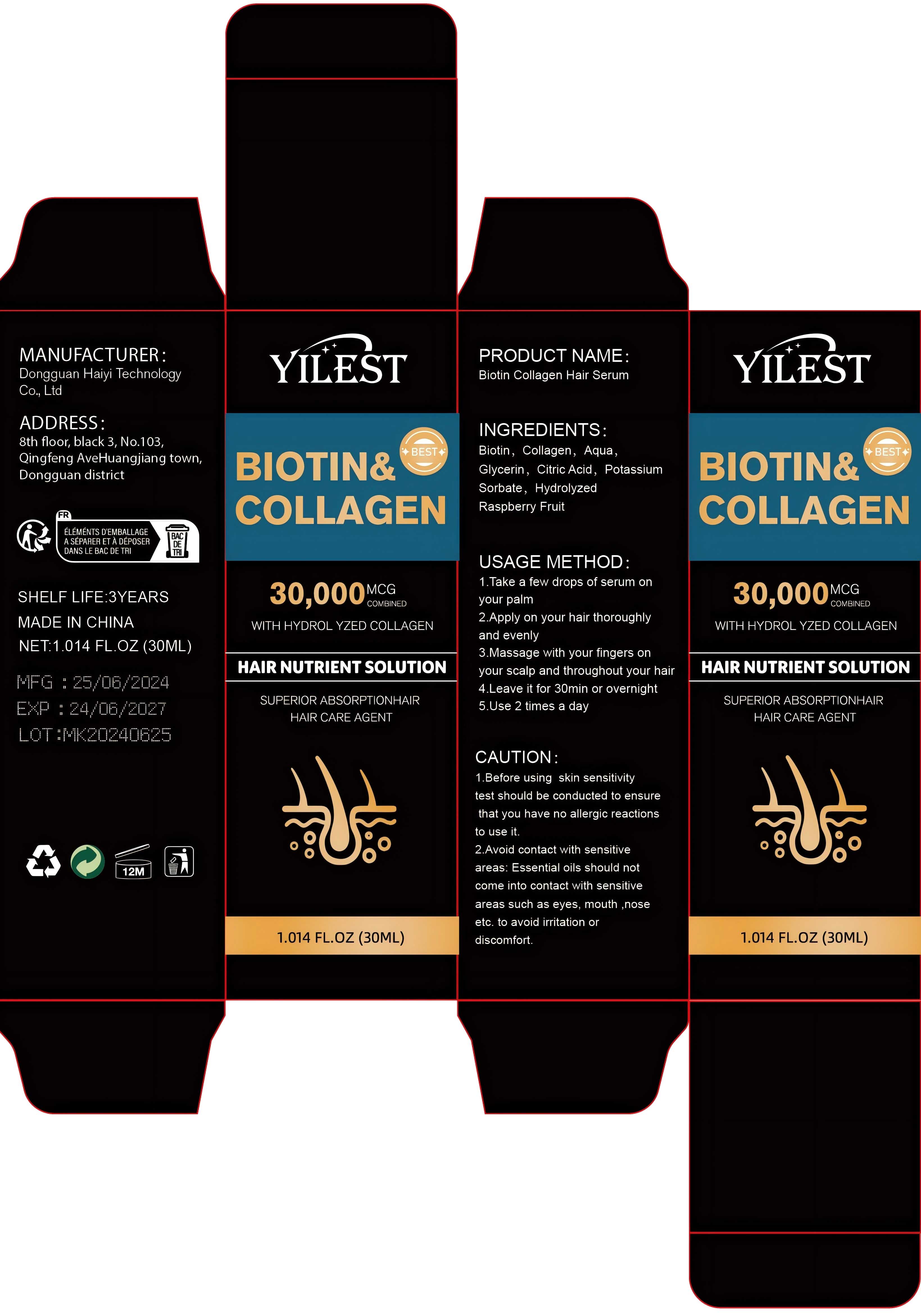 DRUG LABEL: Biotin Collagen Hair Serum
NDC: 84732-074 | Form: OIL
Manufacturer: Dongguan Haiyi Technology Co.,Ltd.
Category: otc | Type: HUMAN OTC DRUG LABEL
Date: 20241030

ACTIVE INGREDIENTS: BIOTIN 1 mg/30 mL
INACTIVE INGREDIENTS: RASPBERRY; POTASSIUM SORBATE; METHYL CARBOXYMETHYLPHENYL AMINOCARBOXYPROPYLPHOSPHONATE; GLYCERIN; CITRIC ACID; WATER

Active ingredient

Biotin

Inactive ingredient

Collagen, Aqua,Glycerin，Citric Acid, Potassium Sorbate, Hydrolyzed Raspberry Fruit

Purpose section

SUPERIOR ABSORPTIONHAIR HAIR CARE AGENT

Warning

1.Before using skin sensitivitytest should be conducted to ensurethat you have no allergic reactionsto use it.

2.Avoid contact with sensitiveareas: Essential oils should notcome into contact with sensitiveareas such as eyes, mouth ,noseetc. to avoid irritation ordiscomfort.

stop use

This product may cause allergic reactions in asmall number of people.
lf you experience any discomfort,please stop using it immediately.

not use

Not suitable for use by children, pregnantor breast feeding people.

OUT OF CHILDREN

KEEP THE PRODUCT OUT OF REACH OF CHILDREN to

HOW TO USE

1.Take a few drops of serum onyour palm

2.Apply on your hair thoroughlyand evenly

3.Massage with your fingers onyour scalp and throughout your hair

4.Leave it for 30min or overnight

5.Use 2 times a day

DOSAGE

Use 2 times a day